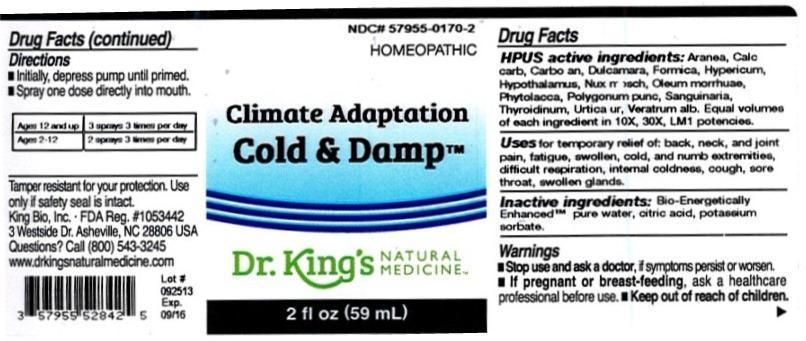 DRUG LABEL: Climate Adaptation Cold and Damp
NDC: 57955-0170 | Form: LIQUID
Manufacturer: King Bio Inc.
Category: homeopathic | Type: HUMAN OTC DRUG LABEL
Date: 20131119

ACTIVE INGREDIENTS: ARANEUS DIADEMATUS 10 [hp_X]/59 mL; OYSTER SHELL CALCIUM CARBONATE, CRUDE 10 [hp_X]/59 mL; CARBO ANIMALIS 10 [hp_X]/59 mL; SOLANUM DULCAMARA TOP 10 [hp_X]/59 mL; FORMICA RUFA 10 [hp_X]/59 mL; HYPERICUM PERFORATUM 10 [hp_X]/59 mL; BOS TAURUS HYPOTHALAMUS 10 [hp_X]/59 mL; NUTMEG 10 [hp_X]/59 mL; COD LIVER OIL 10 [hp_X]/59 mL; PHYTOLACCA AMERICANA ROOT 10 [hp_X]/59 mL; PERSICARIA PUNCTATA 10 [hp_X]/59 mL; SANGUINARIA CANADENSIS ROOT 10 [hp_X]/59 mL; THYROID, UNSPECIFIED 10 [hp_X]/59 mL; URTICA URENS 10 [hp_X]/59 mL; VERATRUM ALBUM ROOT 10 [hp_X]/59 mL
INACTIVE INGREDIENTS: WATER; CITRIC ACID MONOHYDRATE; POTASSIUM SORBATE

Climate Adaptation Cold and Damp™

ACTIVE INGREDIENT

Drug Facts__________________________________________________________________________________________________________

HPUS active ingredients: Aranea diadema, Calcarea carbonica, Carbo animalis, Dulcamara, Formica rufa, Hypericum perforatum, Hypothalamus, Nux moschata, Oleum morrhuae, Phytolacca decandra, Polygonum punctatum, Sanguinaria canadensis, Thyroidinum, Urtica urens, Veratrum album. Equal volumes of each ingredient in 10X, 30X, LM1 potencies.

INDICATIONS AND USAGE

Uses for temporary relief of: back, neck, and joint pain, fatigue, swollen, cold, and numb extremities, difficult respiration, internal coldness, cough, sore throat, swollen glands.

Inactive Ingredients:

Bio-Energetically Enhanced™ pure water, citric acid and potassium sorbate.

Warnings

- Stop use and ask your doctor if symptoms persist or worsen.

- If pregnant or breast-feeding, ask a healthcare professional before use.

- Keep out of reach of children

DOSAGE AND ADMINISTRATION

- Initially, depress pump until primed.
- Spray one dose directly into mouth.
- Ages 12 and up- 3 sprays 3 times per day.
- Ages 2-12- 2 sprays 3 times per day.

OTHER SAFETY INFORMATION

Tamper resistant for your protection. Use only if safety seal is intact.

PURPOSE

Uses for temporary relief of:

- back, neck and joint pain
- fatigue, swollen, cold and numb extremities
- difficult respiration
- internal coldness
- cough
- sore throat
- swollen glands